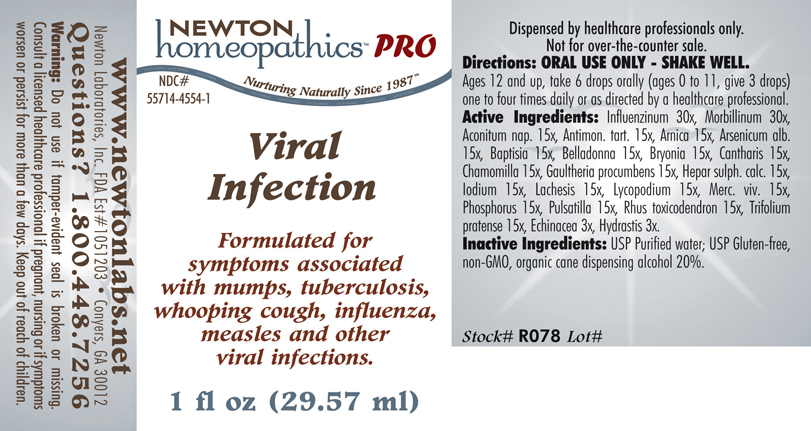 DRUG LABEL: Viral Infection 
NDC: 55714-4554 | Form: LIQUID
Manufacturer: Newton Laboratories, Inc.
Category: homeopathic | Type: HUMAN PRESCRIPTION DRUG LABEL
Date: 20110601

ACTIVE INGREDIENTS: Influenza A Virus 30 [hp_X]/1 mL; Influenza B Virus 30 [hp_X]/1 mL; Measles Virus 30 [hp_X]/1 mL; Aconitum Napellus 15 [hp_X]/1 mL; Antimony Potassium Tartrate 15 [hp_X]/1 mL; Arnica Montana 15 [hp_X]/1 mL; Arsenic Trioxide 15 [hp_X]/1 mL; Baptisia Tinctoria Root 15 [hp_X]/1 mL; Atropa Belladonna 15 [hp_X]/1 mL; Bryonia Alba Root 15 [hp_X]/1 mL; Lytta Vesicatoria 15 [hp_X]/1 mL; Matricaria Recutita 15 [hp_X]/1 mL; Gaultheria Procumbens Top 15 [hp_X]/1 mL; Calcium Sulfide 15 [hp_X]/1 mL; Iodine 15 [hp_X]/1 mL; Lachesis Muta Venom 15 [hp_X]/1 mL; Lycopodium Clavatum Spore 15 [hp_X]/1 mL; Mercury 15 [hp_X]/1 mL; Phosphorus 15 [hp_X]/1 mL; Pulsatilla Vulgaris 15 [hp_X]/1 mL; Toxicodendron Pubescens Leaf 15 [hp_X]/1 mL; Trifolium Pratense Flower 15 [hp_X]/1 mL; Echinacea, Unspecified 3 [hp_X]/1 mL; Goldenseal 3 [hp_X]/1 mL
INACTIVE INGREDIENTS: Alcohol

Viral Infection

INDICATIONS & USAGE SECTION

Viral Infection Formulated for symptoms associated with mumps, tuberculosis, whooping cough, influenza, measles and other viral infections.

DOSAGE & ADMINISTRATION SECTION

Directions: ORAL USE ONLY - SHAKE WELL. Ages 12 and up, take 6 drops orally (ages 0 to 11, give 3 drops) one to four times daily or as directed by a healthcare professional.

ACTIVE INGREDIENT SECTION

Influenzinum 30x, Morbillinum 30x, Aconitum nap. 15x, Antimon. tart. 15x, Arnica 15x, Arsenicum alb. 15x, Baptisia 15x, Belladonna 15x, Bryonia 15x, Cantharis 15x, Chamomilla 15x, Gaultheria procumbens 15x, Hepar sulph. calc.15x, Iodium 15x, Lachesis 15x, Lycopodium 15x, Merc. viv. 15x, Phosphorus 15x, Pulsatilla 15x, Rhus toxicodendron 15x, Trifolium pratense 15x, Echinacea 3x, Hydrastis 3x.

PURPOSE SECTION

Formulated for symptoms associated with mumps, tuberculosis, whooping cough, influenza, measles and other viral infections.

INACTIVE INGREDIENT SECTION

USP Purified water; USP Gluten-free, non-GMO, organic cane dispending alcohol 20%.

QUESTIONS? SECTION

www.newtonlabs.net Newton Laboratories, Inc. FDA Est # 1051203 - Conyers, GA 30012 Questions? 1.800.448.7256

WARNINGS SECTION

Warning: Do not use if tamper - evident seal is broken or missing. Consult a licensed healthcare professional if pregnant, nursing or if symptoms worsen or persist for more than a few days. Keep out of reach of children.

PREGNANCY OR BREAST FEEDING SECTION

Consult a licensed healthcare professional if pregnant, nursing or if symptoms worsen or persist for more than a few days.

KEEP OUT OF REACH OF CHILDREN SECTION

Keep out of reach of children.